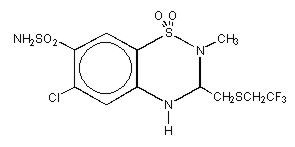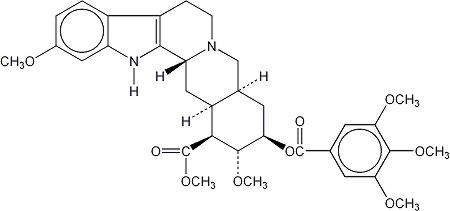 DRUG LABEL: Unknown
Manufacturer: Pfizer Labs
Category: prescription | Type: HUMAN PRESCRIPTION DRUG LABELING
Date: 20060206

RENESE®-R
(polythiazide/reserpine)
Tablets

WARNING

This fixed combination drug is not indicated for initial therapy of hypertension. Hypertension requires therapy titrated to the individual patient. If the fixed combination represents the dosage so determined, its use may be more convenient in patient management. The treatment of hypertension is not static, but must be reevaluated as conditions in each patient warrant.

DESCRIPTION

RENESE®-R tablets combine polythiazide and reserpine, two antihypertensive agents with complementary properties. Each blue, scored tablet of RENESE-R provides:

Renese (polythiazide). . . . . . . . . . . . . . . . . . . . . . . . . . . . . . . . 2.0 mg

Reserpine . . . . . . . . . . . . . . . . . . . . . . . . . . . . . .. . . . . . . . .0.25 mg

RENESE (polythiazide) is a member of the benzothiazide (thiazide) family of diuretic/antihypertensive agents. It is designated chemically as 2H-1,2,4-Benzothiadiazine-7-sulfonamide,6-chloro-3,4-dihydro-2-methyl-3-[[2,2,2-trifluoroethyl)thio]methyl]-,1,1-dioxide with a molecular formula of C11H13ClF3N3O4S3 and a molecular weight of 439.87.

Polythiazide is a white crystalline substance insoluble in water, but readily soluble in alkaline solution, and has the following structural formula:

Reserpine, one of the alkaloids of Rauwolfia serpentina, has the following structural formula:

Reserpine – which is administered orally, is insoluble in water, very slightly soluble in ether, l g in about 1800 mL alcohol and about 6 mL chloroform, slightly soluble in benzene, freely soluble in acetic acid.

It has a molecular weight of 608.69 and its molecular formula is C33H40N2O9. Reserpine is chemically designated as Yohimban-16-carboxylic acid, 11,17-dimethoxy-18-[(3,4,5-trimethoxybenzoyl)oxy]-, methyl ester, (3β,16β,17α,18β,20α)-. It is a white or pale buff to slightly yellowish crystalline powder that is insoluble in water.

Inert Ingredients: FD&C Blue No. 1; dibasic calcium phosphate; lactose; magnesium stearate; polyethylene glycol; sodium lauryl sulfate; starch; vanillin.

CLINICAL PHARMACOLOGY

Polythiazide

Renese (polythiazide) alone has demonstrated clinical effectiveness in lowering elevated blood pressure in patients without visible edema as well as in edematous hypertensive patients. Its mechanism of action results in an interference with the renal tubular mechanism of electrolyte reabsorption. At maximal therapeutic dosage all thiazides are approximately equal in their diuretic potency. The mechanism whereby thiazides function in the control of hypertension is unknown. Polythiazide is well absorbed following oral administration with diuresis beginning approximately 2 hours later. Peak human plasma concentrations occur about 5 hours after ingestion. Polythiazide is removed slowly thereafter with a plasma elimination half-life of approximately 27 hours. One-fifth of the drug is recovered unchanged in human urine; the remainder is cleared via feces and as metabolites. Animal studies indicate metabolism occurs by rupture of the thiadiazine ring and loss of the side chain.

Reserpine

Reserpine has several complementary actions of benefit to the hypertensive patient, including a calming effect and a slowing of the pulse rate.

Depletion of norepinephrine from tissue receptor sites is thought to be responsible for the decrease in peripheral vascular resistance and subsequent fall in blood pressure. Bradycardia is usually associated with this effect.

The tranquilizing effect of reserpine is apparently due to serotonin and catecholamine depletion in the brain.

Sympathetic inhibition produced by reserpine also may result in vasodilation and increased cutaneous blood flow with resulting flushing, feeling of warmth, or nasal congestion. Increased parasympathomimetic activity may produce increased gastrointestinal motility, increased gastric acid secretion and miosis.

Reserpine is absorbed orally and is widely distributed in body tissues, especially adipose tissue. A study in a small number of normal subjects who received a radioactively labeled 0.25 mg dose of reserpine showed a biphasic half-life of 4.5 hours during the first phase, and 11.3 days during the second phase. The full therapeutic effects of reserpine may not be seen for 2–3 weeks.

Reserpine is extensively metabolized to inactive compounds. It is slowly excreted via the urine and feces.

Reserpine crosses the blood-brain barrier and the placenta, and appears in cord blood.

Since polythiazide reduces or eliminates the sodium and fluid retention frequently associated with hypertension, it enhances the efficacy of reserpine in lowering elevated blood pressure. RENESE-R often has been found to be more effective than equivalent doses of either agent alone. Both the cardiovascular and central nervous system effects may persist following withdrawal of the drug.

INDICATIONS AND USAGE

Hypertension (see box warning).

Usage in Pregnancy

The routine use of diuretics in an otherwise healthy woman is inappropriate and exposes mother and fetus to unnecessary hazard. Diuretics do not prevent development of toxemia of pregnancy, and there is no satisfactory evidence that they are useful in the treatment of developed toxemia.

Edema during pregnancy may arise from pathological causes or from the physiologic and mechanical consequences of pregnancy. Thiazides are indicated in pregnancy when edema is due to pathologic causes, just as they are in the absence of pregnancy (however, see Precautions/Pregnancy section). Dependent edema in pregnancy, resulting from restriction of venous return by the expanded uterus, is properly treated through elevation of the lower extremities and use of support hose; use of diuretics to lower intravascular volume in this case is illogical and unnecessary. There is hypervolemia during normal pregnancy which is harmful to neither the fetus nor the mother (in the absence of cardiovascular disease), but which is associated with edema – including generalized edema, in the majority of pregnant women. If this edema produces discomfort, increased recumbency will often provide relief. In rare instances, this edema may cause extreme discomfort which is not relieved by rest. In these cases, a short course of diuretics may provide relief and may be appropriate.

CONTRAINDICATIONS

A. Related to polythiazide

1. Advanced renal or hepatic failure.
2. Hypersensitivity to this or other sulfonamide derivatives.

B. Related to reserpine

1. Demonstrated hypersensitivity.
2. Patients with a history of mental depression.
3. Demonstrated peptic ulcer or ulcerative colitis.

WARNINGS

Serum electrolyte determinations are especially indicated for patients with severe derangement of metabolic processes, e.g., surgery, vomiting, or parenteral fluid therapy. Electrolyte imbalance may be caused by certain diseases such as cirrhosis, or it may result from drug therapy, such as therapy with corticosteroids. Patients with cirrhosis who are continually receiving RENESE-R should be observed carefully for the development of hepatic precoma or coma. Indications of impending hepatic failure are tremor, confusion, drowsiness, and hepatic fetor.

Thiazides may precipitate kidney failure and uremia in patients with pre-existing renal pathology and impaired renal function.

Available information tends to implicate all oral dosage forms of potassium salts ingested in solid form with or without thiazides in the etiology of nonspecific, small bowel lesions consisting of ulceration with or without stenosis, causing obstruction, hemorrhage and perforation, and frequently requiring surgery. Deaths due to these complications have been reported. All oral dosage forms of potassium salts ingested in solid form should be used only when adequate dietary supplementation is not practical, and should be discontinued immediately if abdominal pain, distention, nausea, vomiting, or gastrointestinal bleeding occur.

RENESE-R does not itself contain enteric-coated potassium.

Electroshock therapy should not be given within one week of cessation of reserpine.

Reserpine may cause mental depression. Recognition of depression may be difficult because this condition may often be disguised by somatic complaints (Masked Depression). The drug should be discontinued at first signs of depression such as despondency, early morning insomnia, loss of appetite, impotence, or self-deprecation. Drug-induced depression may persist for several months after drug withdrawal and may be severe enough to result in suicide.

PRECAUTIONS

General

Polythiazide

Since all diuretic agents may reduce serum levels of sodium, chloride, and potassium – especially with brisk diuresis or when used concurrently with steroids – patients should be observed regularly for early signs of fluid or electrolyte imbalance, and serum electrolyte studies should be performed periodically. Warning signs of possible electrolyte imbalance, irrespective of cause include fatigue, muscle cramps, gastrointestinal disturbances, lethargy, oliguria, and tachycardia. In extreme cases, hypotension, shock, and coma may develop. Frequently, serum electrolyte levels do not correlate with signs or symptoms of electrolyte imbalance. Unduly restricted salt intake as well as concurrent administration of digitalis may exaggerate metabolic effects of hypokalemia. A favorable ratio of potassium to sodium excretion lessens the possibility of hypokalemia. However, should this occur or be suspected, foods with a high potassium content (bananas, apricots, citrus fruits, prune juice, etc.) should be given. When necessary, oral potassium supplements may be administered. If other antihypertensive agents are used concurrently, lower than usual doses of RENESE-R and of the other agents should be considered.

The antihypertensive effects of the drug may be enhanced in the postsympathectomy patient.

Reserpine

Since reserpine may increase gastric acid secretion, it should be used cautiously in patients with a history of peptic ulcer or ulcerative colitis. Extreme caution is needed in patients with a history of mental depression, and reserpine should be discontinued at the first sign of depressive symptoms. Parkinsonism and confusion have been encountered, particularly in psychiatric patients, and constitute an indication for withdrawal of the drug. Caution should be exercised when treating patients with impairment of renal function, as lowered blood pressure may result in further decompensation and embarrassment of function.

Discontinue the drug one to two weeks prior to elective surgery since an unexpected degree of hypotension and bradycardia have been reported in patients receiving anesthetic agents concurrently with reserpine, probably due to a reduced responsiveness to norepinephrine. For emergency surgical procedures vagal blocking agents may be given parenterally to prevent or reverse hypotension and/or bradycardia. Reserpine may cause increased appetite and weight gain in some patients.

Information for Patients

Since RENESE-R may increase urination, it is advisable to take it early during the day. If stomach upset occurs, take the drug with food or milk.

Notify your physician if muscle weakness, cramps, nausea, or dizziness occur as these may indicate the loss of too much potassium from your body.

A few people who take this medicine may be more sensitive to sunlight than they are normally. Avoid too much sun or use of a sunlamp until you see how you react.

RENESE-R may cause drowsiness. Make sure you know how you react before driving, using machinery, or performing tasks that require alertness.

Notify your physician if changes in mood or sleep patterns occur. Dizziness or lightheadedness may occur when getting up from a sitting or lying position. Getting up slowly may help. Notify your physician if the problem worsens.

Laboratory Tests

Determination of serum electrolytes to detect possible electrolyte imbalance should be performed at appropriate intervals.

Drug Interactions

Polythiazide

Thiazides may add to or potentiate the action of other antihypertensive drugs. Potentiation occurs with ganglionic or peripheral adrenergic blocking drugs.

Hypokalemia may be more likely to develop during concomitant use of corticosteroids or ACTH. Diuretic-induced hypokalemia may precipitate digitalis toxicity.

Thiazide drugs may augment the paralyzing actions of tubocurarine, and may decrease the arterial responsiveness to norepinephrine. Extra precautions may be necessary in patients who may require these drugs or their derivatives, as in surgery.

Dosage adjustment of antidiabetic agents is frequently indicated during thiazide administration. Indomethacin may partially antagonize the hypotensive effect of the thiazide diuretics. Generally, do not give lithium with diuretics because they reduce lithiums renal clearance and add a high risk of lithium toxicity.

Quinidine, a weak base, may have its half-life prolonged by concomitant administration of thiazide diuretics which alkalinize the urine.

Sulfonamides may potentiate the action of the thiazide diuretics, possibly by displacement from binding sites on plasma albumin.

Orthostatic hypotension may be aggravated by the use of alcohol, barbiturates, or narcotics with thiazide diuretics.

Reserpine

Reserpine should be used cautiously with digitalis or quinidine as the concurrent use may enhance the appearance of arrhythmias.

Additive CNS depressant effects may occur when reserpine is administered concomitantly with other CNS depressants such as barbiturates and alcohol.

Concomitant administration of reserpine and levodopa has been reported to reduce the patient's response to levodopa. Reserpine should be avoided in patients receiving levodopa.

The effects of indirect-acting sympathomimetic amines such as ephedrine may be decreased.

Patients who are receiving monoamine oxidase inhibitors may experience excitation and hypertension when reserpine is added. The combination should be avoided.

Reserpine may add to the pharmacologic effects of beta-adrenergic blocking agents (i.e., CNS depression and cardiovascular effects).

Drug/Laboratory Test Interactions

Polythiazide

The thiazides may alter various laboratory test results. These include all electrolytes, particularly potassium, BUN, glucose, and PBI. Thiazides may decrease serum PBI levels without signs of thyroid disturbance.

Like other thiazide diuretics, polythiazide may cause a rise in serum uric acid levels with or without overt symptoms of gout.

Reserpine

Chronic administration results in a decrease in urinary catecholamines and vanilmandelic acid excretion.

Interference with colorimetric assay procedures for the determination of urinary 17-hydroxycorticosteroids by the Glenn-Nelson technique and 17-ketosteroids by the Holtorff Koch modification of the Zimmerman reaction have been reported.

Animal Tumorigenicity

Although long-term studies in animals have not been conducted with RENESE-R, rodent studies have shown that reserpine is an animal tumorigen, causing an increased incidence of mammary fibroadenomas in female mice, malignant tumors of the seminal vesicles in male mice, and malignant adrenal medullary tumors in male rats. These findings arose in 2 year studies in which the drug was administered in the feed at concentrations of 5 and 10 ppm—about 100 to 300 times the usual human dose. The breast neoplasms are thought to be related to reserpine's prolactin-elevating effect.

Several other prolactin-elevating drugs have also been associated with an increased incidence of mammary neoplasia in rodents.

The extent to which these findings indicate a risk to humans is uncertain. Tissue culture experiments show that about one-third of human breast tumors are prolactin-dependent in vitro, a factor of considerable importance if the use of the drug is contemplated in a patient with previously detected breast cancer. The possibility of an increased risk of breast cancer in reserpine users has been studied extensively; however, no firm conclusion has emerged. Although a few epidemiologic studies have suggested a slightly increased risk (less than twofold in all studies except one) in women who have used reserpine, other studies of generally similar design have not confirmed this. Epidemiologic studies conducted using other drugs (neuroleptic agents) that, like reserpine, increase prolactin levels and therefore would be considered rodent mammary carcinogens, have not shown an association between chronic administration of the drug and human mammary tumorigenesis. While long-term clinical observation has not suggested such an association, the available evidence is considered too limited to be conclusive at this time. An association of reserpine intake with pheochromocytoma or tumors of the seminal vesicles has not been explored.

Pregnancy

Teratogenic Effects

Pregnancy Category C

Animal reproduction studies have not been conducted with RENESE-R. There are no adequate and well controlled studies in pregnant women. It is also not known whether RENESE-R can cause fetal harm when administered to a pregnant woman or can affect reproduction capacity. RENESE-R should be given to a pregnant woman only if clearly needed.

Nonteratogenic Effects

Thiazides cross the placental barrier and appear in cord blood. When polythiazide and reserpine are used in women of childbearing age, the potential benefits of this drug combination should be weighed against the possible hazards to the fetus. The hazards include fetal or neonatal jaundice, thrombocytopenia, and possible other adverse reactions which have occurred in the adult.

Nursing Mothers

Thiazides and reserpine appear in breast milk. Because of the potential for serious adverse reactions in nursing infants from RENESE-R, a decision should be made whether to discontinue nursing or to discontinue the drug, taking into account the importance of the drug to the mother.

Pediatric Use

Safety and effectiveness in children have not been established.

ADVERSE REACTIONS

The following adverse reactions have been observed, but there is not enough systemic collection of data to support an estimate of their frequency.

Polythiazide

The most common reactions associated with polythiazide therapy are weakness and dizziness, but seldom require cessation of therapy. Weakness is reported in less than 3% of patients receiving the drug, and dizziness is reported in less than 2% of patients. These can be overcome by reducing the dose or taking measures to improve electrolytic balance.

Other reactions, reported to occur in less than 1% of patients, are:

Gastrointestinal: nausea, gastrointestinal disturbances, reversible cholestatic jaundice, necrotizing angiitis, pancreatitis.

Dermatological: maculopapular skin rash, photosensitivity.

Central Nervous System: vertigo, paresthesia, fatigue, headache.

Cardiovascular: orthostatic hypotension.

EENT: xanthopsia.

Hematological: Leukopenia (neutropenia), agranulocytosis, and aplastic anemia have been reported with the older thiazides but not with the newer compounds such as polythiazide. Purpura (with or without thrombocytopenia) has been reported with polythiazide.

Reserpine

The most common reactions associated with reserpine therapy, dizziness and drowsiness, are reported in less than 2% of patients. Reactions to reserpine are usually reversible and disappear when the drug is discontinued.

Other reactions, occurring in less than 1% of patients on reserpine are:

Gastrointestinal: hypersecretion, nausea, vomiting, diarrhea, anorexia, dry mouth.

Dermatological: rash, pruritus, purpura.

Central Nervous System: depression, nervousness, paradoxical anxiety, nightmares, headache, and rare Parkinsonian syndrome to CNS sensitization manifested by deafness, glaucoma, uveitis, and optic atrophy.

Cardiovascular: angina-like symptoms, arrhythmias particularly when used concurrently with digitalis or quinidine, flushing of the skin, and bradycardia.

EENT: nasal congestion, miosis.

Sexual Difficulties: impotence or decreased libido.

OVERDOSAGE

One case of RENESE-R overdosage is reported after ingestion of an unknown number of tablets. Electrolyte replacement therapy was successful in treating the symptoms.

Polythiazide

An overdose of Renese may cause electrolyte imbalance, manifested by fatigue, muscle weakness, cramps, gastrointestinal disturbances, lethargy, tachycardia, and/or other arrhythmias, and hypotension.

Should overdosage with Renese occur, electrolyte balance and adequate hydration should be maintained. Gastric lavage is recommended followed by supportive treatment. Where necessary, this may include intravenous dextrose and saline with potassium and other electrolyte therapy, administered with caution as indicated by laboratory testing at appropriate intervals.

Reserpine

Signs of overdosage include CNS depression ranging from drowsiness to coma, bradycardia and hypotension, respiratory depression, hypothermia, diarrhea, vomiting, mental depression, skin flushing, miosis, and extrapyramidal signs such as stiffness and tremors. Emesis or gastric lavage to remove unabsorbed drug is of benefit in conscious patients, even if several hours have elapsed since ingestion. Treatment is symptomatic and supportive.

Parasympathomimetic side effects usually can be controlled with small doses of atropine or other anticholinergics. Evidence of motor dysfunction often can be controlled by drugs useful for parkinsonism. Avoid vasopressor drugs (except in cases of extreme hypotension) and rapid intravenous infusions because of the uncertain cardiac status.

It is not known whether dialysis would be of benefit in treating cases of overdosage of RENESE-R.

DOSAGE AND ADMINISTRATION

As determined by individual titration (see box warning).

Initial dosages of the combination should conform to those dosages of the individual components established during titration.

Maintenance dosages range from ½ tablet to 2 tablets daily. Dosage of other antihypertensive agents, particularly ganglionic blockers, that are used concomitantly should be reduced.

HOW SUPPLIED

RENESE-R tablets (2 mg polythiazide–0.25 mg reserpine) are available as blue scored tablets,

tablet code 446, in bottles of 100 (NDC 0069-4460 -66) and 1,000

(NDC-0069-4460-82). RENESE-R should be stored at room temperature. Dispense in tight,
light-resistant container.

Rx only

Distributed by:

Pfizer Labs

Division of Pfizer, Inc, NY, NY 10017

69-1200-00-3

September 1995